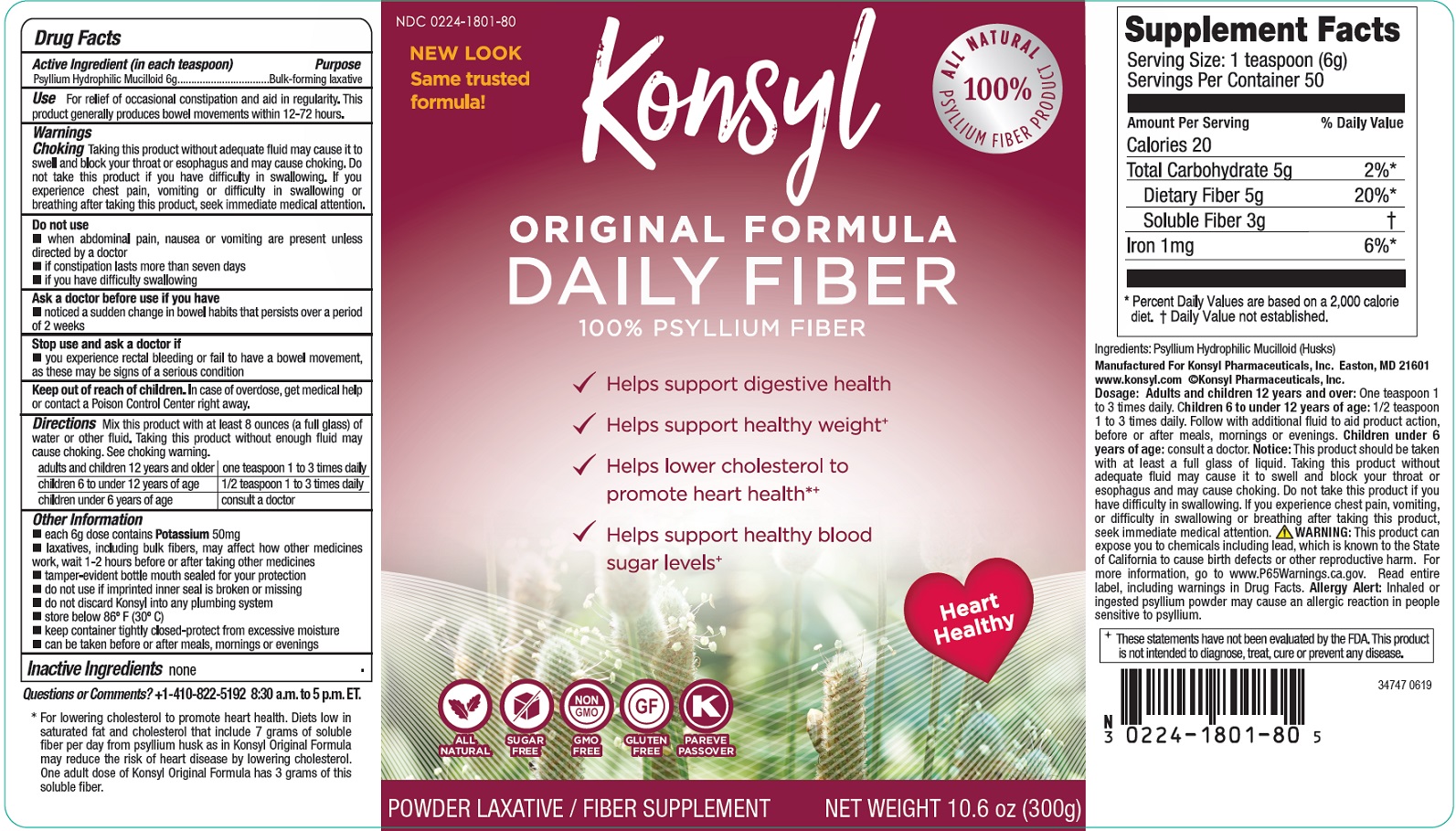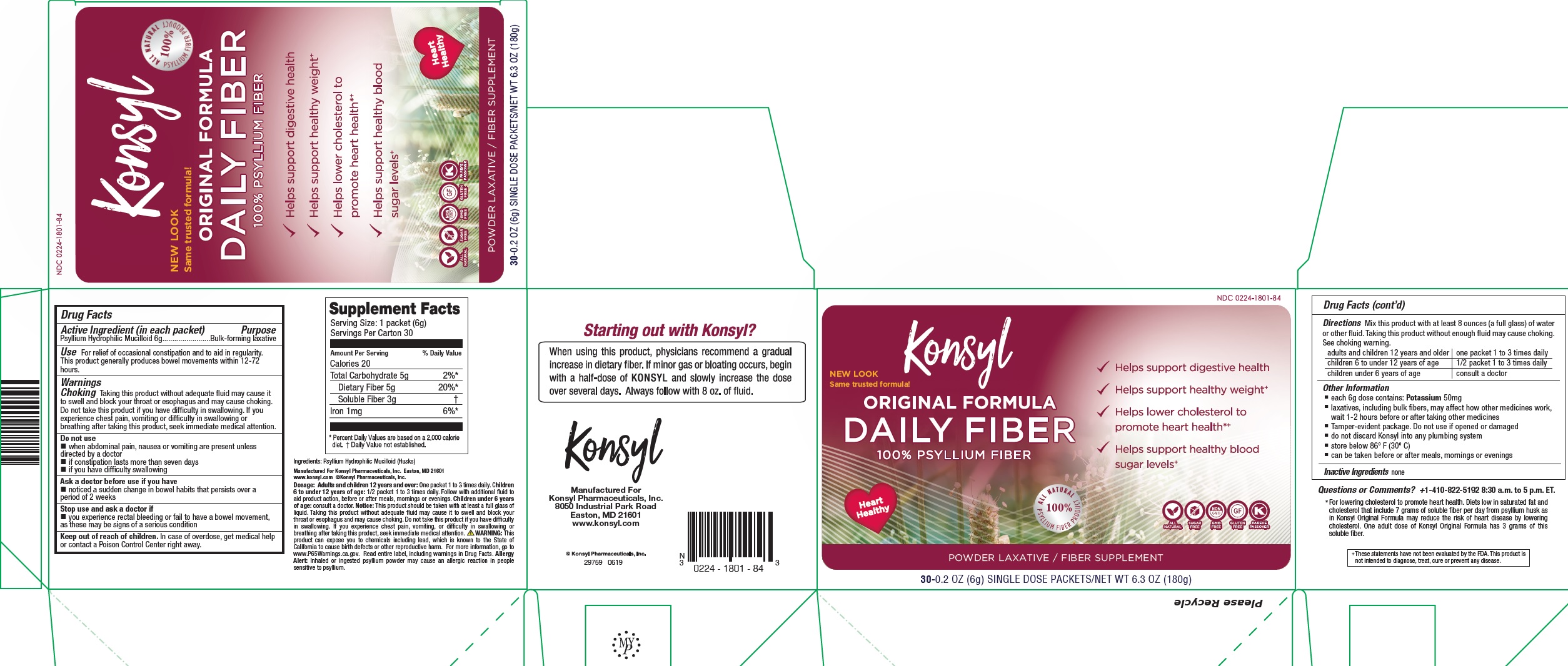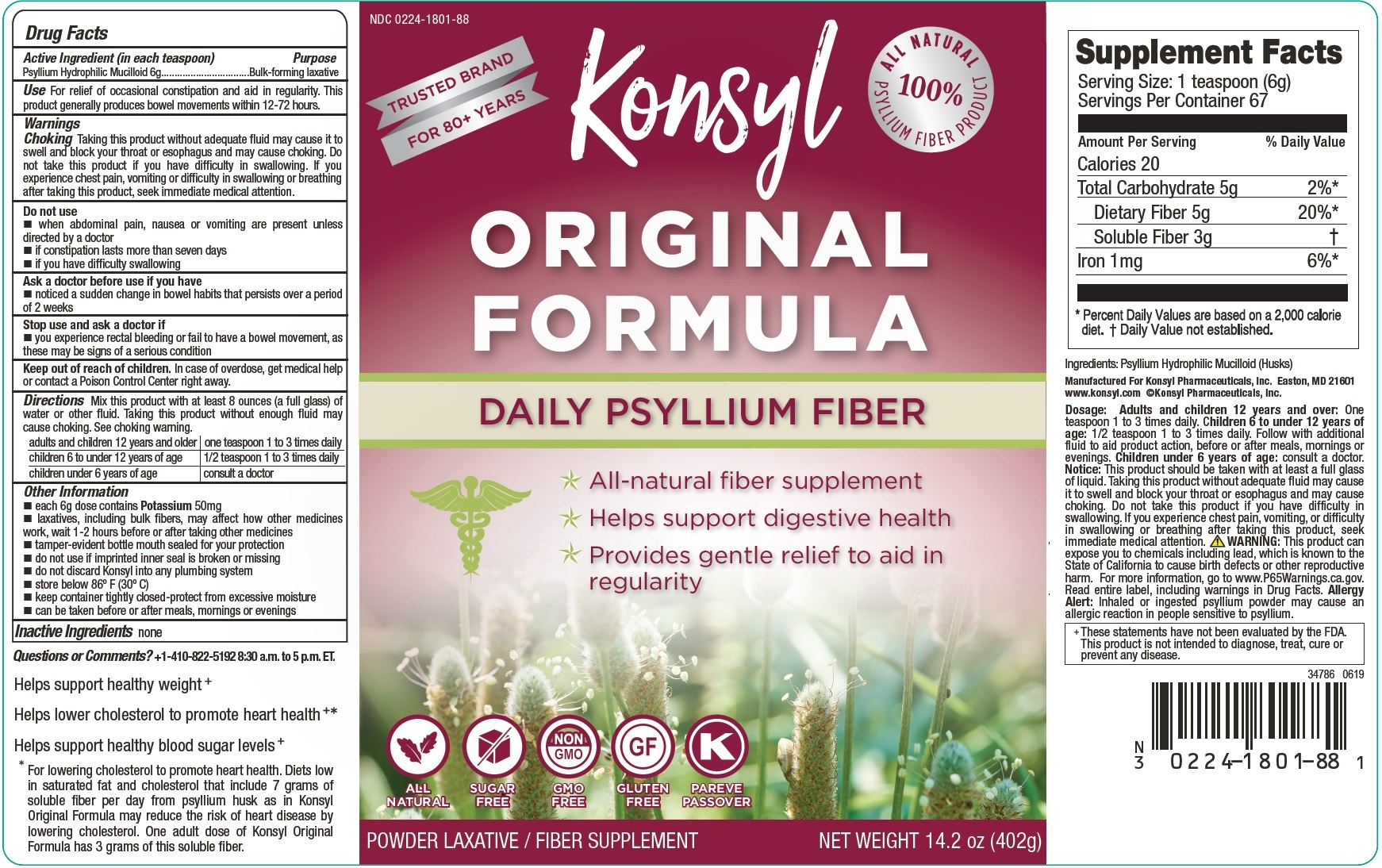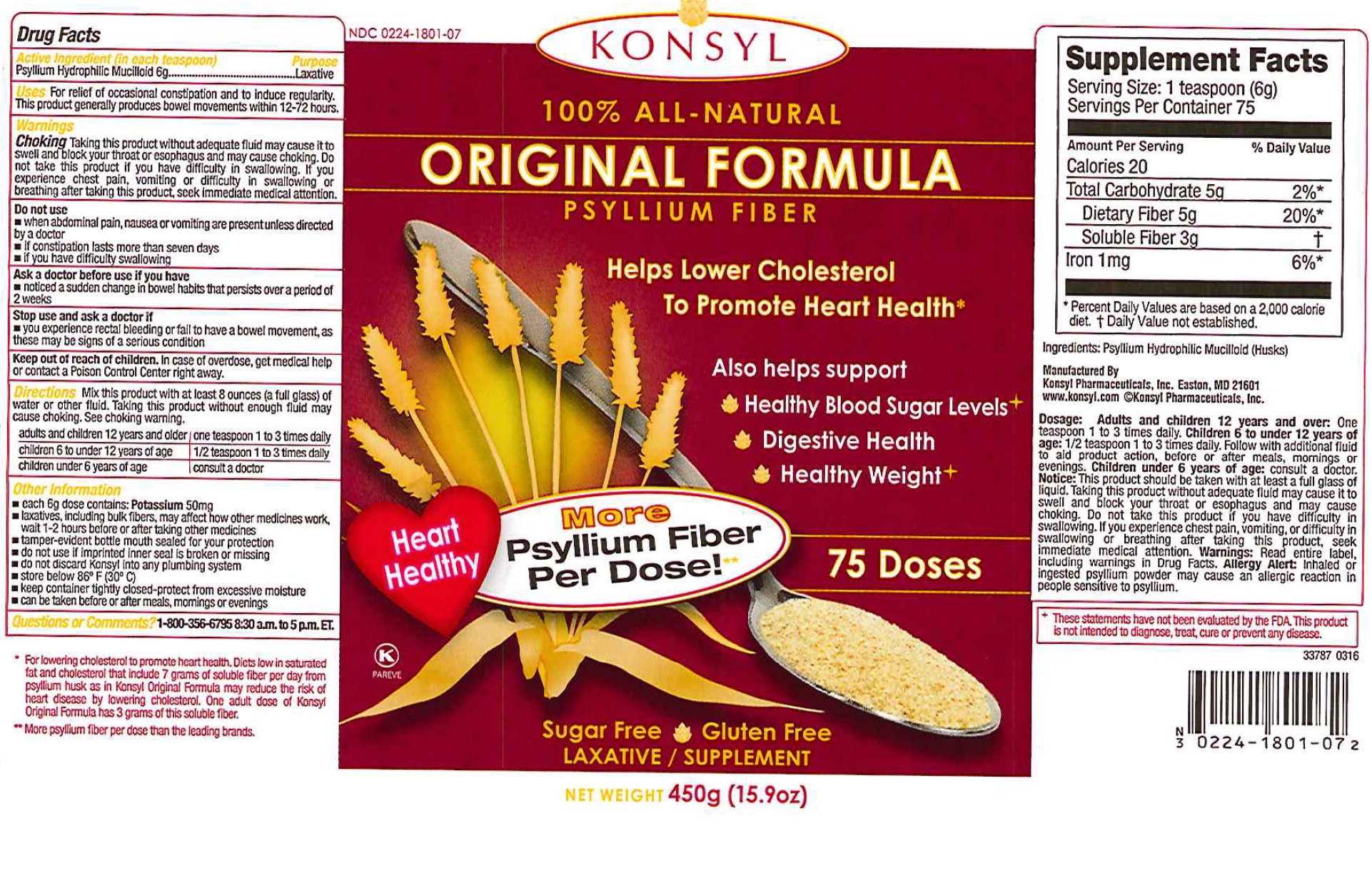 DRUG LABEL: KONSYL Original Formula Psyllium Fiber
NDC: 0224-1801 | Form: GRANULE
Manufacturer: Konsyl Pharmaceuticals, Inc.
Category: otc | Type: HUMAN OTC DRUG LABEL
Date: 20240112

ACTIVE INGREDIENTS: PSYLLIUM HUSK 6 g/6 g

Konsyl Original Formula Psyllium Fiber

Active Ingredients (in each teaspoon)

Psyllium Hydrophilic Mucilloid 6g

Purpose

Laxative

Uses

For relief of occasional constipation and to induce regularity.

This product generally produces bowel movements within 12-72 hours.

Warnings

Choking Taking this product without adequate fluid may cause it to swell and block your throat or esophagus and may cause choking. Do not take this product if you have difficulty in swallowing. If you experience chest pain, vomiting or difficulty in swallowing or breathing after taking this product, seek immediate medical attention.

Do not use

- when abdominal pain, nausea or vomiting are present unless directed by a doctor.
- if constipation lasts more than seven days
- if you have difficulty swallowing

Ask a doctor before use if you have

- noticed a sudden change in bowel habits that persists over a period of 2 weeks

Stop use and ask a doctor if

- you experience rectal bleeding or fail to have a bowel movement, as these may be signs of a serious condition

Keep out of reach of children.

In case of overdose, get medical help or contact a Poison Control Center right away

Directions

Mix this product with at least 8 ounces (a full glass) of water or other fluid. Taking this product without enough fluid may cause choking. See choking warning.

adults and children 12 years and older |one teaspoon 1 to 3 times daily

children 6 to under 12 years of age | 1/2 teaspoon 1 to 3 times daily

children under 6 years of age | consult a doctor

Other Information

- each 6g dose contains: Potassium 50mg
- laxatives, including bulk fibers, may affect how other other medicines work, wait 1-2 hours before or after taking other medicines
- tamper-evident bottle mouth sealed for your protection
- do not use if imprinted inner seal is broken or missing
- do not discard Konsyl into any plumbing system
- store below 86 degrees F (30 degrees C)
- keep container tightly closed-protect from excessive moisture
- can be taken before or after meals, mornings or evenings

Inactive Ingredients

none

Questions or comments?

- 1-800-356-6795 8:30 a.m to 5 p.m. ET.